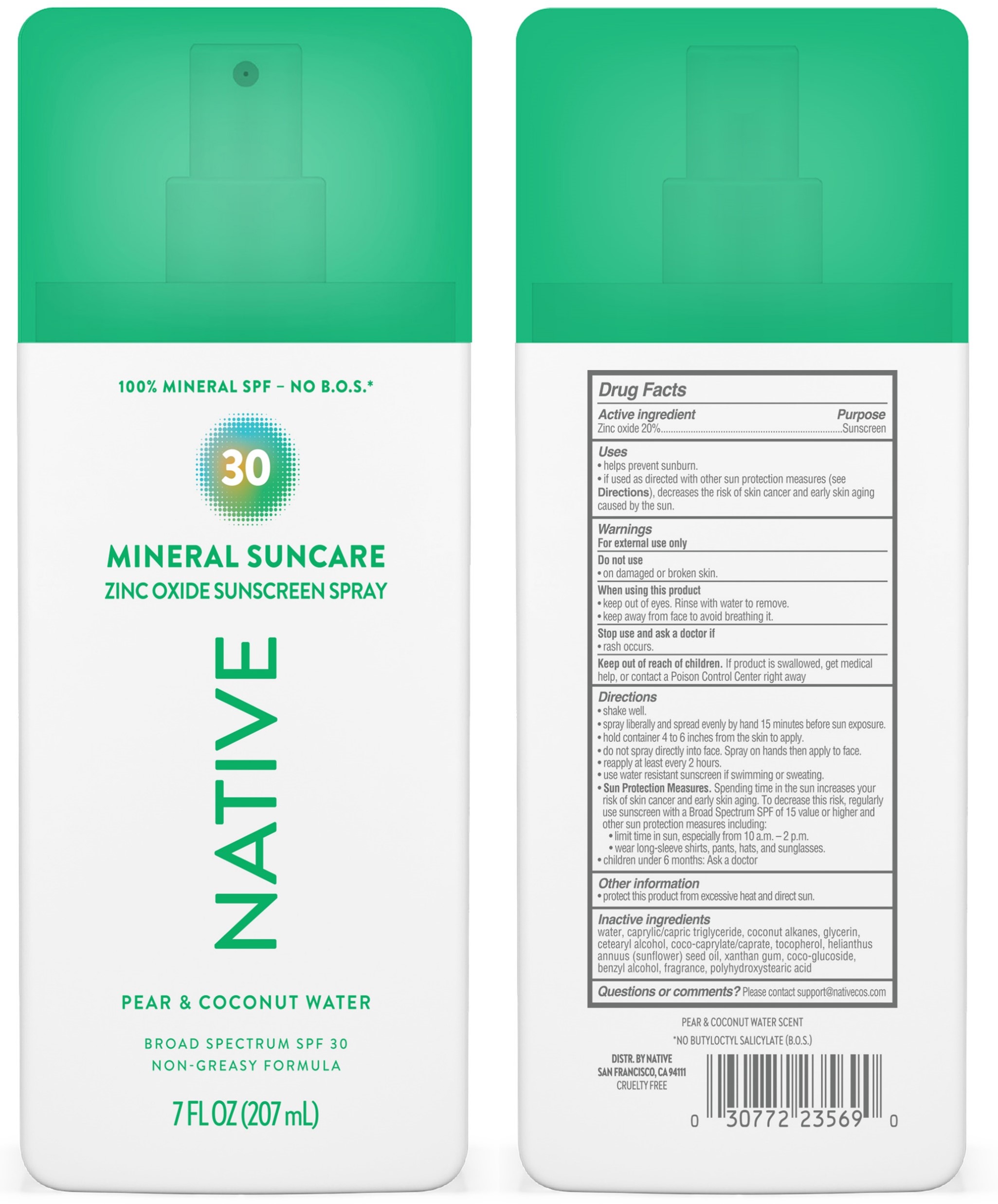 DRUG LABEL: Native Mineral Suncare Zinc Oxide Sunscreen Pear and Coconut Water Broad Spectrum SPF 30
NDC: 64412-5507 | Form: SPRAY
Manufacturer: Twincraft Inc.
Category: otc | Type: HUMAN OTC DRUG LABEL
Date: 20251217

ACTIVE INGREDIENTS: ZINC OXIDE 20 g/100 mL
INACTIVE INGREDIENTS: COCONUT ALKANES; COCO GLUCOSIDE; COCO-CAPRYLATE/CAPRATE; WATER; GLYCERIN; TOCOPHEROL; CETEARYL ALCOHOL; POLYHYDROXYSTEARIC ACID (2300 MW); CAPRYLIC/CAPRIC TRIGLYCERIDE; SUNFLOWER OIL; BENZYL ALCOHOL; XANTHAN GUM

Native Mineral Suncare Zinc Oxide Sunscreen Spray Pear and Coconut WaterBroad Spectrum SPF 30

Drug Facts

ACTIVE INGREDIENT

ZINC OXIDE 20%

PURPOSE

Sunscreen

Uses

- helps prevent sunburn
- if used as directed with other sun protection measures (see Directions), decreases the risk of skin cancer and early skin aging caused by the sun

WARNINGS

For external use only

Do not use

- on damaged or broken skin

When using this product

- keep out of eyes. Rinse with water to remove.
- keep away from face to avoid breahing it.

Stop use and ask a doctor if

rash occurs.

Keep out of reach of children

If product is swallowed, get medical help, or contact a Poison Control Center right away.

Directions

- shake well
- spray liberally and spread evenly by hand 15 minutes before sun exposure
- hold container 4 to 6 inches from the skin to apply
- do not spray directly into face. Spray on hands then apply to face
- reapply at least every 2 hours
- use water resistant sunscreen if swimming or sweating
- Sun Protection Measures.Spending time in the sun increases your risk of skin cancer and early skin aging. To decrease this risk, regularly use a sunscreen with a Broad Spectrum SPF value of 15 or higher and other sun protection measures including:
  - limit time in sun, especially from 10 a.m. – 2 p.m.
  - wear long-sleeved shirts, pants, hats, and sunglasses
- children under 6 months: ask a doctor

Other information

- protect this product from excessive heat and direct sun

Inactive ingredients

water, caprylic/capric triglyceride, coconut alkanes, glycerin, cetearyl alcohol, coco-caprylate/caprate, tocopherol, helianthus annuus (sunflower) seed oil, xanthan gum, coco-glucoside, benzyl alcohol, fragrance, polyhydroxystearic acid

Distr. by Native San Francisco, CA 94111

Questions or comments?

Please contact support#\@nativecos.com

PRINCIPAL DISPLAY PANEL - 208 mL Bottle, Pump

30

MINERAL SUNCARE

ZINC OXIDE SUNSCREEN SPRAY

NATIVE

PEAR & COCONUT WATER

BROAD SPECTRUM SPF 30

7 FL OZ (207 mL)